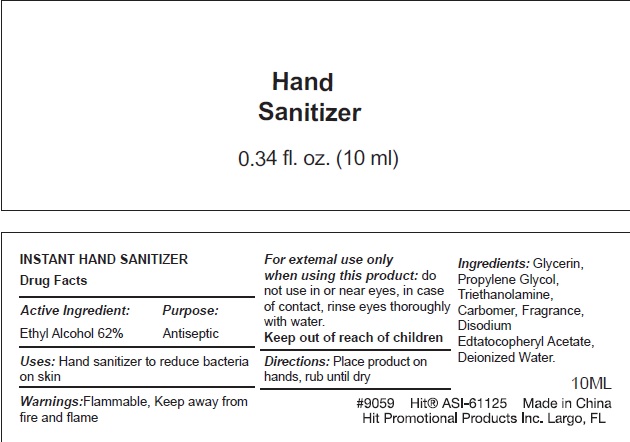 DRUG LABEL: HAND SANITIZER
NDC: 75613-005 | Form: GEL
Manufacturer: Ningbo Lanzi Cosmetic Technology Co., Ltd
Category: otc | Type: HUMAN OTC DRUG LABEL
Date: 20200623

ACTIVE INGREDIENTS: ALCOHOL 62 mL/100 mL
INACTIVE INGREDIENTS: WATER; PROPYLENE GLYCOL; EDETATE DISODIUM; TROLAMINE; .ALPHA.-TOCOPHEROL ACETATE, D-; GLYCERIN

HAND SANITIZER

Active ingredient

Ethyl Alcohol 62%

Purpose

Antiseptic

Use

hand sanitizing to reduce bacteria on skin.

Warnings

For external use only

Flammable. Keep away from fire and flame.

When using this product

do not use in or near eyes. In case of contact, rinse eyes thoroughly with water.

Keep out of reach of children.

If swallowed, get medical help or contact a Poison Control Center right away.

Directions

Place product on hands, rub until dry.

Inactive ingredients

Glycerin, Propylene Glycol, Triethanolamine, Carbomer, Fragrance, Disodium edtatocopheryl acetate, Deionized Water